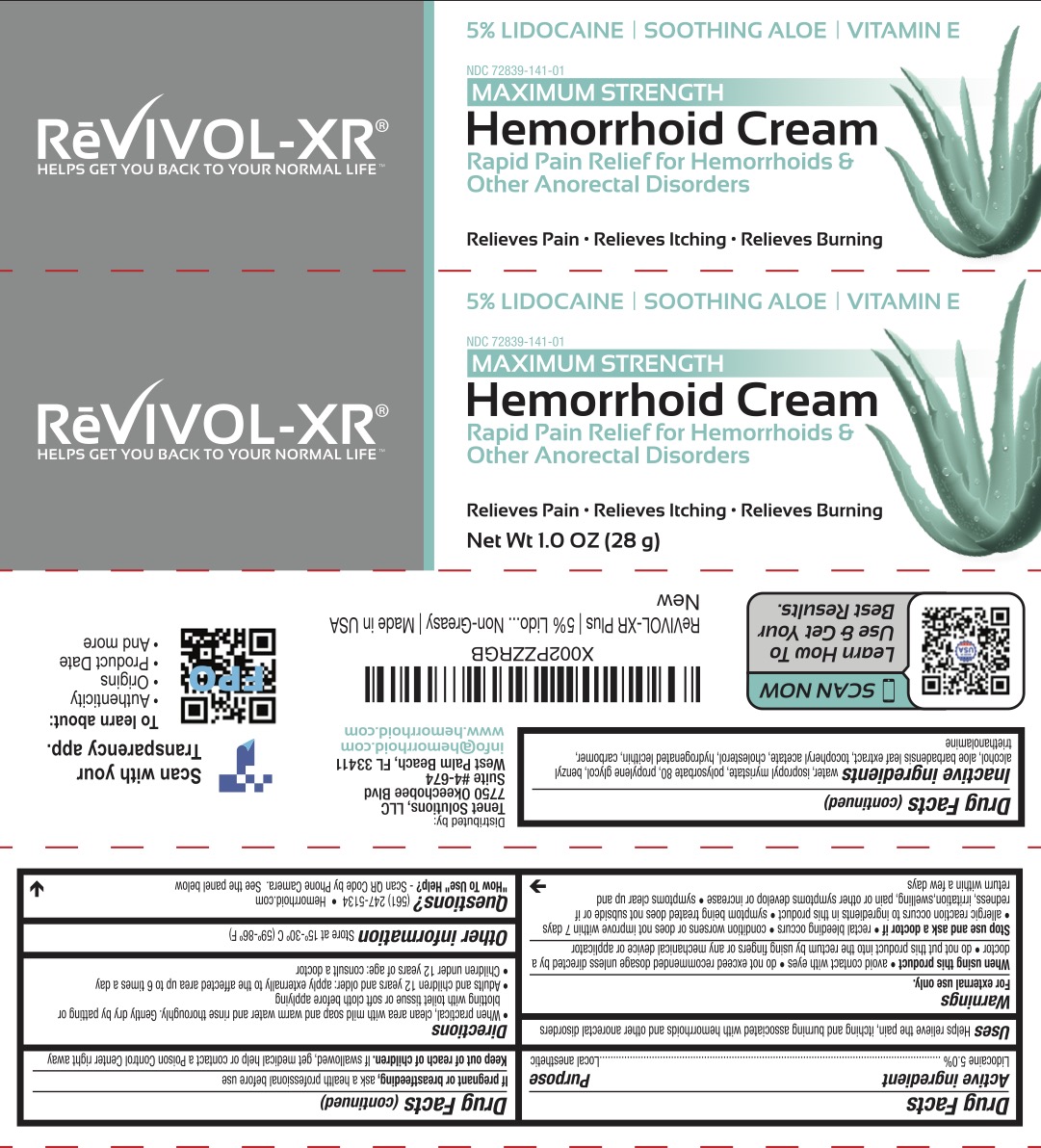 DRUG LABEL: Rectal Care Cream
NDC: 72839-141 | Form: CREAM
Manufacturer: Derma Care Research Labs
Category: otc | Type: HUMAN OTC DRUG LABEL
Date: 20241219

ACTIVE INGREDIENTS: LIDOCAINE 5 g/100 g
INACTIVE INGREDIENTS: CHOLESTEROL; HYDROGENATED SOYBEAN LECITHIN; ISOPROPYL MYRISTATE; PROPYLENE GLYCOL; WATER; TROLAMINE; .ALPHA.-TOCOPHEROL ACETATE; ALOE VERA LEAF; BENZYL ALCOHOL; CARBOMER 940; POLYSORBATE 80

Rectal Care

ACTIVE INGREDIENT

Lidocaine 5.0%

PURPOSE

Local Anesthetic

Uses

Helps relieve the pain, itching, and burning associated with hemorrhoids and other anorectal disorders.

WARNINGS

For external use only.

When using this product avoid contact with eyes, do not exceed recommended dosage unless directed by a doctor, do not put this product into the rectum by using fingers or any mechanical device or applicator.

Stop use and ask a doctor if rectal bleeding occurs, condition worsens or does not improve within 7 days, allergic reaction occurs to ingredients in this product, symptom being treated does not subside or if redness, irritation, swelling, pain or other symptoms develop or increase, or symptoms clear up and return within a few days.

KEEP OUT OF REACH OF CHILDREN

Keep out of reach of the children. If swallowed, get medical help or contact a Poison Control Center right away.

DOSAGE AND ADMINISTRATION

- When practical, clean area with mild soap and warm water and rinse thoroughly. Gently dry by patting or blotting with toilet tissue or a soft cloth before applying.
- Adults and children 12 years and older: apply externally to the affected area up to 6 times a day.
- Children under 12 years of age: consult a doctor.
- To use finger cots: roll one finger cot over a finger. Gently squeeze cream onto finger cot. Smooth a layer of the cream over the affected area

INACTIVE INGREDIENT

Aloe Barbadensis Leaf Extract, Benzyl Alcohol, Carbomer, Cholesterol, Hydrogenated Lecithin, Isopropyl Myristate, Polysorbate 80, Propylene Glycol, Tocopheryl Acetate, Triethanolamine, Water